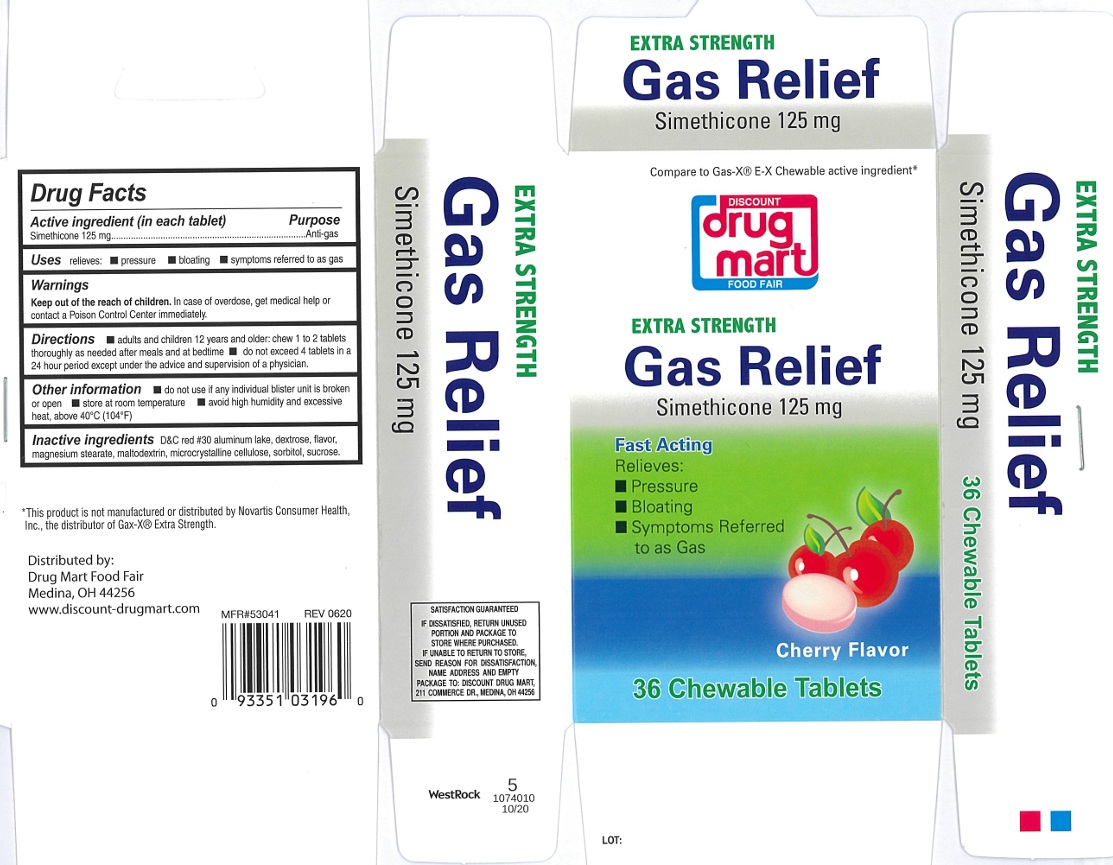 DRUG LABEL: Extra Strength Gas Relief Cherry Flavor
NDC: 53943-134 | Form: TABLET, CHEWABLE
Manufacturer: Discount Drug Mart, Inc
Category: otc | Type: Human OTC Drug Label
Date: 20250224

ACTIVE INGREDIENTS: DIMETHICONE 125 mg/1 1
INACTIVE INGREDIENTS: D&C RED NO. 30 ALUMINUM LAKE; MAGNESIUM STEARATE; CELLULOSE, MICROCRYSTALLINE; SORBITOL; SUCROSE; MALTODEXTRIN; DEXTROSE, UNSPECIFIED FORM

Extra Strength Gas Relief

ACTIVE INGREDIENT(S)

Simethicone 125 mg

PURPOSE

Anti-gas

USE(S)

relieves:

- Pressure
- bloating
- Symptoms referred to as gas

WARNINGS

.

KEEP OUT OF THE REACH OF CHILDREN.

In case of overdose, get medical help or contact a poison Control Centre immediately.

DIRECTIONS

- adults and children 12 years and older: chew 1 to 2 tablets thoroughly as needed after meals and at bedtime
- do not exceed 4 tablets in a 24 hour period except under the advice and supervision of a physician.

OTHER INFORMATION

- do not use if any individual blister unit is broken or open
- store at room temperature
- avoid high humidity and excessive heat, above 40ºC (104ºF)

INACTIVE INGREDIENTS

D&C red #30 aluminum lake, dextrose, flavor, magnesium stearate, maltodextrin, microcrystalline cellulose, sorbitol, sucrose.

PRINCIPAL DISPLAY PANEL

Compare to Gas-X® E-X Chewable active ingredient*

NDC 53943-134-39

DISCOUNT drug mart

FOOD FAIR

EXTRA STRENGTH

Gas Relief

Simethicone 125 mg

Fast Acting

Relieves:

- Pressure
- Bloating
- Symptoms Referred to as Gas

Cherry Flavor

36chewable tablets